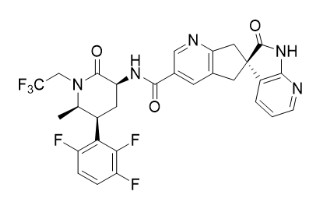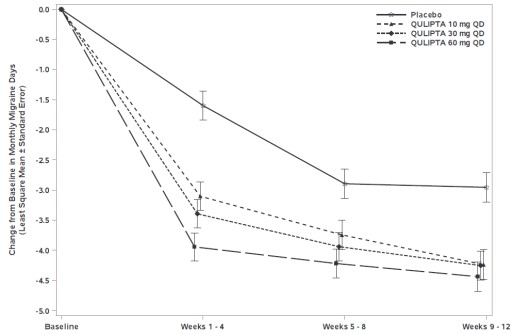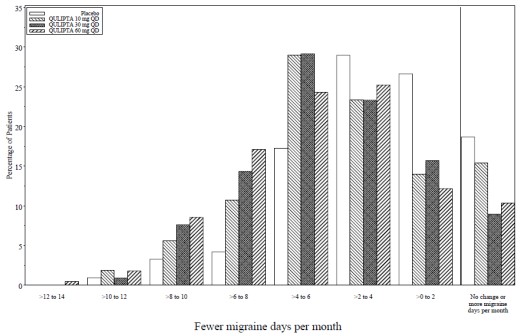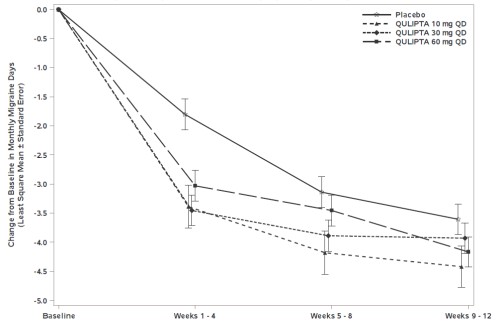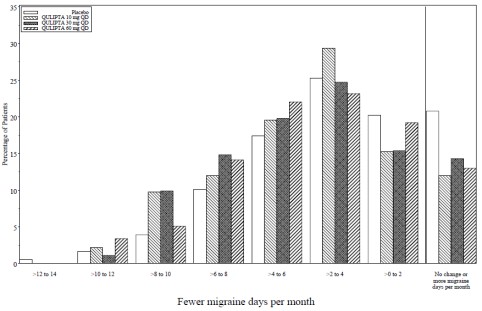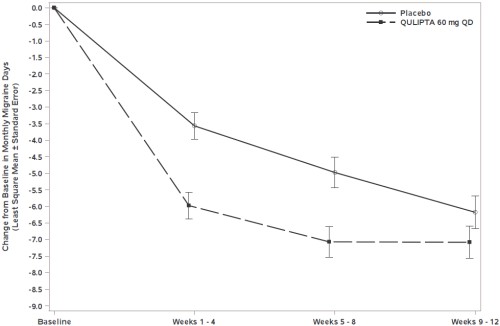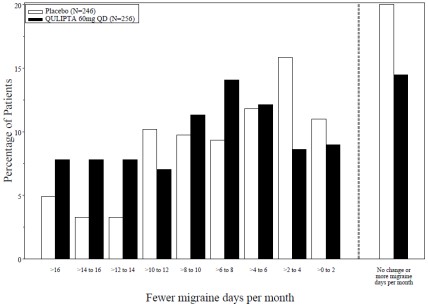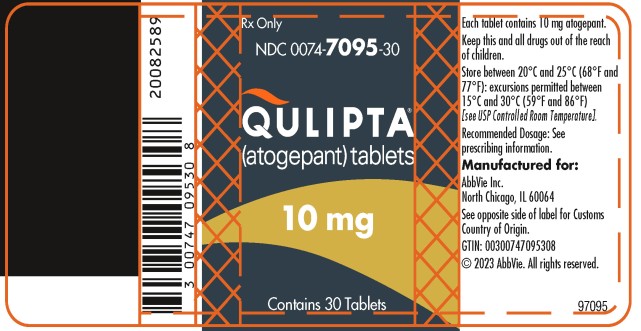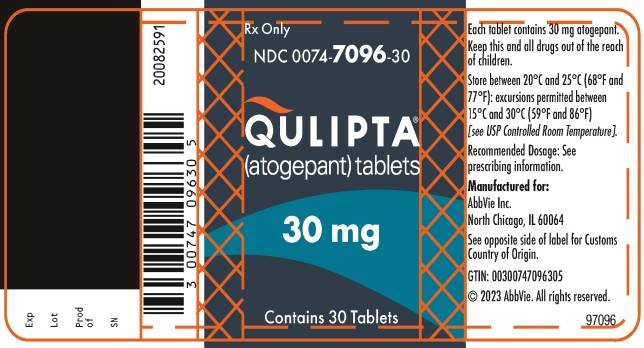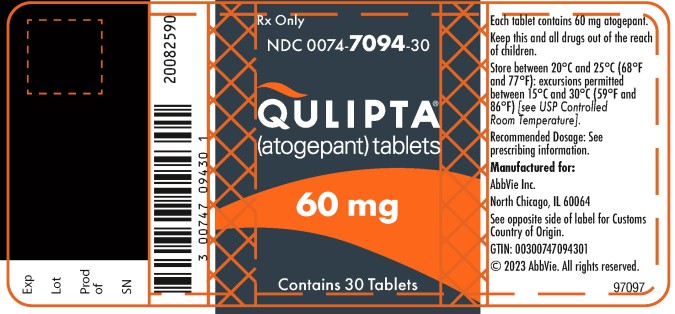 DRUG LABEL: Qulipta
NDC: 0074-7095 | Form: TABLET
Manufacturer: AbbVie Inc.
Category: prescription | Type: HUMAN PRESCRIPTION DRUG LABEL
Date: 20250930

ACTIVE INGREDIENTS: ATOGEPANT 10 mg/1 1
INACTIVE INGREDIENTS: SILICON DIOXIDE; CROSCARMELLOSE SODIUM; MANNITOL; MICROCRYSTALLINE CELLULOSE; COPOVIDONE K25-31; SODIUM CHLORIDE; SODIUM STEARYL FUMARATE; VITAMIN E POLYETHYLENE GLYCOL SUCCINATE

HIGHLIGHTS OF PRESCRIBING INFORMATION

These highlights do not include all the information needed to use QULIPTA safely and effectively. See full prescribing information for QULIPTA.
QULIPTA® (atogepant) tablets, for oral use
Initial U.S. Approval: 2021

RECENT MAJOR CHANGES

Dosage and Administration (2.2) | 9/2025
Warnings and Precautions (5.2, 5.3) | 3/2025

1 INDICATIONS AND USAGE

QULIPTA is a calcitonin gene-related peptide receptor antagonist indicated for the preventive treatment of migraine in adults. (1)

2 DOSAGE AND ADMINISTRATION

- QULIPTA is taken orally with or without food. (2.1)
- For episodic migraine, the recommended dosage is 10 mg, 30 mg, or 60 mg taken once daily. (2.1)
- For chronic migraine, the recommended dosage is 60 mg taken once daily. (2.1)
- Severe Renal Impairment or End-Stage Renal Disease (2.2, 8.6):
  - Episodic migraine: 10 mg once daily.
  - Chronic migraine: Not recommended.

3 DOSAGE FORMS AND STRENGTHS

Tablets: 10 mg, 30 mg, and 60 mg. (3)

4 CONTRAINDICATIONS

Patients with a history of hypersensitivity to atogepant or to any of the components of QULIPTA. (4)

5 WARNINGS AND PRECAUTIONS

- Hypersensitivity Reactions: If a hypersensitivity reaction occurs, discontinue QULIPTA and initiate appropriate therapy. Severe hypersensitivity reactions have included anaphylaxis and dyspnea. These reactions can occur days after administration. (5.1)
- Hypertension: New-onset or worsening of pre-existing hypertension may occur. (5.2)
- Raynaud’s phenomenon: New-onset or worsening of pre-existing Raynaud’s phenomenon may occur. (5.3)

6 ADVERSE REACTIONS

The most common adverse reactions (at least 4% and greater than placebo) are nausea, constipation, and fatigue/somnolence. (6.1)

To report SUSPECTED ADVERSE REACTIONS, contact AbbVie at 1-800-678-1605 or FDA at 1-800-FDA-1088 or www.fda.gov/medwatch.

7 DRUG INTERACTIONS

Recommended dosage modifications:

- Strong CYP3A4 Inhibitors (2.2, 7.1):
  - Episodic or chronic migraine: 10 mg once daily

- Strong CYP3A4 Inducers (2.2, 7.2):
  - Episodic migraine: 60 mg once daily (monitor for reduced efficacy).
  - Chronic migraine: Not recommended.

- Moderate CYP3A4 Inducers (2.2, 7.2):
  - Episodic migraine: 60 mg once daily.
  - Chronic migraine: Not recommended.

- Weak CYP3A4 Inducers (2.2, 7.2):
  - Episodic migraine: 30 mg or 60 mg once daily.
  - Chronic migraine: 60 mg once daily.

- OATP Inhibitors (2.2, 7.3):
  - Episodic migraine: 10 mg or 30 mg once daily.
  - Chronic migraine: 30 mg once daily.

8 USE IN SPECIFIC POPULATIONS

- Pregnancy: Based on animal data, may cause fetal harm. (8.1)
- Avoid use in patients with severe hepatic impairment. (8.7)

FULL PRESCRIBING INFORMATION

1 INDICATIONS AND USAGE

QULIPTA is indicated for the preventive treatment of migraine in adults.

2 DOSAGE AND ADMINISTRATION

2.1 Recommended Dosage

QULIPTA is taken orally with or without food.

Episodic Migraine

The recommended dosage of QULIPTA for episodic migraine is 10 mg, 30 mg, or 60 mg taken once daily.

Chronic Migraine

The recommended dosage of QULIPTA for chronic migraine is 60 mg taken once daily.

2.2 Dosage Modifications

Dosage modifications and usage recommendations for episodic and chronic migraine with concomitant use of specific drugs and for patients with renal impairment are provided in Table 1.

Table 1: Dosage Modifications for Drug Interactions and for Specific Populations

Dosage Modifications | Recommended Once Daily Dosage for Episodic Migraine | Usage and Recommended Once Daily Dosage for Chronic Migraine
Concomitant Drug [see Drug Interactions (7)]
Strong CYP3A4 Inhibitors (7.1) | 10 mg | 10 mg
Strong CYP3A4 Inducers (7.2) | 60 mga | Not recommended
Moderate CYP3A4 Inducers (7.2) | 60 mg | Not recommended
Weak CYP3A4 Inducers (7.2) | 30 mg or 60 mg | 60 mga
OATP Inhibitors (7.3) | 10 mg or 30 mg | 30 mg
Renal Impairment [see Use in Specific Populations (8)]
Severe Renal Impairment and End-Stage Renal Disease (CLcr <30 mL/min) (8.6) | 10 mg | Not recommended

a Coadministration decreases atogepant exposure. Monitor for reduced efficacy.

3 DOSAGE FORMS AND STRENGTHS

QULIPTA 10 mg is supplied as white to off-white, round biconvex tablets debossed with “A” and “10” on one side.

QULIPTA 30 mg is supplied as white to off-white, oval biconvex tablets debossed with “A30” on one side.

QULIPTA 60 mg is supplied as white to off-white, oval biconvex tablets debossed with “A60” on one side.

4 CONTRAINDICATIONS

QULIPTA is contraindicated in patients with a history of hypersensitivity to atogepant or any of the components of QULIPTA. Reactions have included anaphylaxis and dyspnea [see Warnings and Precautions (5.1)].

5 WARNINGS AND PRECAUTIONS

5.1 Hypersensitivity Reactions

Hypersensitivity reactions, including anaphylaxis, dyspnea, rash, pruritus, urticaria, and facial edema, have been reported with use of QULIPTA [see Adverse Reactions (6.2)]. Hypersensitivity reactions can occur days after administration. If a hypersensitivity reaction occurs, discontinue QULIPTA and institute appropriate therapy [see Contraindications (4)].

5.2 Hypertension

Development of hypertension and worsening of pre-existing hypertension have been reported following the use of CGRP antagonists, including QULIPTA, in the postmarketing setting. Some of the patients who developed new-onset hypertension had risk factors for hypertension. There were cases requiring initiation of pharmacological treatment for hypertension and, in some cases, hospitalization. Hypertension may occur at any time during treatment, but was most frequently reported within 7 days of therapy initiation. QULIPTA was discontinued in many of the reported cases.

Monitor patients treated with QULIPTA for new-onset hypertension, or worsening of pre-existing hypertension, and consider whether discontinuation of QULIPTA is warranted if evaluation fails to establish an alternative etiology or blood pressure is inadequately controlled.

5.3 Raynaud’s Phenomenon

Development of Raynaud’s phenomenon and recurrence or worsening of pre-existing Raynaud’s phenomenon have been reported in the postmarketing setting following the use of CGRP antagonists, including QULIPTA. In reported cases with small molecule CGRP antagonists, symptom onset occurred a median of 1.5 days following dosing. Many of the cases reported serious outcomes, including hospitalizations and disability, generally related to debilitating pain. In most reported cases, discontinuation of the CGRP antagonist resulted in resolution of symptoms.

QULIPTA should be discontinued if signs or symptoms of Raynaud’s phenomenon develop, and patients should be evaluated by a healthcare provider if symptoms do not resolve. Patients with a history of Raynaud’s phenomenon should be monitored for, and informed about the possibility of, worsening or recurrence of signs and symptoms.

6 ADVERSE REACTIONS

The following clinically significant adverse reactions are described elsewhere in the labeling:

- Hypersensitivity Reactions [see Warnings and Precautions (5.1)]
- Hypertension [see Warnings and Precautions (5.2)]
- Raynaud’s Phenomenon [see Warnings and Precautions (5.3)]

6.1 Clinical Trials Experience

Because clinical trials are conducted under widely varying conditions, adverse reaction rates observed in the clinical trials of a drug cannot be directly compared to rates in the clinical trials of another drug and may not reflect the rates observed in practice.

The safety of QULIPTA was evaluated in 2657 patients with migraine who received at least one dose of QULIPTA. Of these, 1225 patients were exposed to QULIPTA for at least 6 months, and 826 patients were exposed for 12 months.

In the 12-week, placebo-controlled clinical studies (Studies 1, 2, and 3), 314 patients received at least one dose of QULIPTA 10 mg once daily, 411 patients received at least one dose of QULIPTA 30 mg once daily, 678 patients received at least one dose of QULIPTA 60 mg once daily, and 663 patients received placebo [see Clinical Studies (14)]. Approximately 88% were female, 75% were White, 13% were Black, 10% were Asian, and 10% were of Hispanic or Latino ethnicity. The mean age at study entry was 41 years (range 18 to 74 years).

The most common adverse reactions (incidence at least 4% and greater than placebo) are nausea, constipation, and fatigue/somnolence.

Table 2 summarizes the adverse reactions that occurred during Studies 1, 2, and 3.

Table 2: Adverse Reactions Occurring with an Incidence of At Least 2% for QULIPTA and Greater than Placebo in Studies 1, 2, and 3*
 | Placebo (N= 663) % | QULIPTA 10 mg (N=314) % | QULIPTA 30 mg (N=411) % | QULIPTA 60 mg (N=678) %
Nausea | 3 | 5 | 6 | 9
Constipation | 2 | 6 | 6 | 8
Fatigue/Somnolence | 4 | 4 | 4 | 5
Decreased Appetite | <1 | 2 | 1 | 3
Dizziness | 2 | 2 | 2 | 3

* 10 mg and 30 mg incidence from Studies 1 and 2; 60 mg pooled incidence from Studies 1, 2, and 3.

The adverse reactions that most commonly led to discontinuation of QULIPTA in these studies were nausea (0.6%), constipation (0.5%), and fatigue/somnolence (0.2%).

Liver Enzyme Elevations

In Study 1, Study 2, and Study 3, the rate of transaminase elevations over 3 times the upper limit of normal was similar between patients treated with QULIPTA (0.9%) and those treated with placebo (1.2%). However, there were cases with transaminase elevations over 3 times the upper limit of normal that were temporally associated with QULIPTA treatment; these were asymptomatic and resolved within 8 weeks of discontinuation. There were no cases of severe liver injury or jaundice.

Decreases in Body Weight

In Study 1, Study 2, and Study 3, the proportion of patients with a weight decrease of at least 7% at any point was 2.5% for placebo, 3.8% for QULIPTA 10 mg, 3.2% for QULIPTA 30 mg, and 5.3% for QULIPTA 60 mg.

6.2 Postmarketing Experience

The following adverse reactions have been identified during post approval use of QULIPTA. Because these reactions are reported voluntarily from a population of uncertain size, it is not always possible to estimate their frequency or establish a causal relationship to drug exposure.

Immune System Disorders: Hypersensitivity (e.g., anaphylaxis, dyspnea, rash, pruritus, urticaria, facial edema) [see Contraindications (4) and Warnings and Precautions (5.1)]

Vascular Disorders: Hypertension [see Warnings and Precautions (5.2)], Raynaud’s phenomenon [see Warnings and Precautions (5.3)]

7 DRUG INTERACTIONS

7.1 CYP3A4 Inhibitors

Coadministration of QULIPTA with itraconazole, a strong CYP3A4 inhibitor, resulted in a significant increase in exposure of atogepant in healthy subjects [see Clinical Pharmacology (12.3)]. The recommended dosage of QULIPTA with concomitant use of strong CYP3A4 inhibitors is 10 mg once daily [see Dosage and Administration (2.2)]. No dosage adjustment of QULIPTA is needed with concomitant use of moderate or weak CYP3A4 inhibitors.

7.2 CYP3A4 Inducers

Coadministration of QULIPTA with steady-state rifampin, a strong CYP3A4 inducer and OATP1B1 and OATP1B3 inhibitor, resulted in a significant decrease in exposure of atogepant in healthy subjects [see Clinical Pharmacology (12.3)]. Concomitant administration of QULIPTA with moderate inducers of CYP3A4 can also result in decreased exposure of atogepant. Coadministration of QULIPTA with steady-state topiramate, a weak CYP3A4 inducer, resulted in decreased exposure of atogepant in healthy subjects [see Clinical Pharmacology (12.3)].

For episodic migraine, the recommended dosage of QULIPTA with concomitant use of strong or moderate CYP3A4 inducers is 60 mg once daily. During concomitant use of QULIPTA with strong CYP3A4 inducers, monitor monthly for signs of reduced efficacy, and consider alternative therapies if a reduction in efficacy is observed. The recommended dosage of QULIPTA with concomitant use of weak CYP3A4 inducers is 30 mg or 60 mg once daily [see Dosage and Administration (2.2)].

For chronic migraine, concomitant use of strong or moderate CYP3A4 inducers with QULIPTA is not recommended. The recommended dosage of QULIPTA with concomitant use of weak CYP3A4 inducers is 60 mg once daily. Monitor monthly for signs of reduced efficacy, and consider alternative therapies if a reduction in efficacy is observed [see Dosage and Administration (2.2)].

7.3 OATP Inhibitors

Coadministration of QULIPTA with single dose rifampin, an OATP inhibitor, resulted in a significant increase in exposure of atogepant in healthy subjects [see Clinical Pharmacology (12.3)]. For episodic migraine, the recommended dosage of QULIPTA with concomitant use of OATP inhibitors is 10 mg or 30 mg once daily. For chronic migraine, the recommended dosage of QULIPTA with concomitant use of OATP inhibitors is 30 mg once daily [see Dosage and Administration (2.2)].

8 USE IN SPECIFIC POPULATIONS

8.1 Pregnancy

Pregnancy Exposure Registry

There is a pregnancy exposure registry that monitors outcomes in women who become pregnant while taking QULIPTA. Patients should be encouraged to enroll by calling 1-833-277-0206 or visiting http://empresspregnancyregistry.com.

Risk Summary

There are no adequate data on the developmental risk associated with the use of QULIPTA in pregnant women. In animal studies, oral administration of atogepant during the period of organogenesis (rats and rabbits) or throughout pregnancy and lactation (rats) resulted in adverse developmental effects (decreased fetal and offspring body weight in rats; increased incidence of fetal structural variations in rabbits) at exposures greater than those used clinically [see Data].

In the U.S. general population, the estimated background risk of major birth defects and miscarriages in clinically recognized pregnancies is 2-4% and 15-20%, respectively. The estimated rate of major birth defects (2.2%-2.9%) and miscarriage (17%) among deliveries to women with migraine are similar to rates reported in women without migraine.

Clinical Considerations

Disease-Associated Maternal and/or Embryo/Fetal Risk

Published data have suggested that women with migraine may be at increased risk of preeclampsia and gestational hypertension during pregnancy.

Data

Animal Data

Oral administration of atogepant (0, 5, 15, 125, or 750 mg/kg/day) to pregnant rats during the period of organogenesis resulted in decreases in fetal body weight and in skeletal ossification at the two highest doses tested (125 and 750 mg/kg), which were not associated with maternal toxicity. At the no-effect dose (15 mg/kg/day) for adverse effects on embryofetal development, plasma exposure (AUC) was approximately 4 times that in humans at the maximum recommended human dose (MRHD) of 60 mg/day.

Oral administration of atogepant (0, 30, 90, or 130 mg/kg/day) to pregnant rabbits during the period of organogenesis resulted in an increase in fetal visceral and skeletal variations at the highest dose tested (130 mg/kg/day), which was associated with minimal maternal toxicity. At the no-effect dose (90 mg/kg/day) for adverse effects on embryofetal development, plasma exposure (AUC) was approximately 3 times that in humans at the MRHD.

Oral administration of atogepant (0, 15, 45, or 125 mg/kg/day) to rats throughout gestation and lactation resulted in decreased pup body weight at the highest dose tested (125 mg/kg/day), which persisted into adulthood. At the no-effect dose (45 mg/kg/day) for adverse effects on pre- and postnatal development, plasma exposure (AUC) was approximately 5 times that in humans at the MRHD.

8.2 Lactation

Risk Summary

Data from a lactation study in twelve healthy adult females indicate that atogepant is excreted in breast milk in low amounts. The estimated relative infant dose is approximately 0.19% of the maternal weight-adjusted dose, and the milk-to-plasma ratio is 0.08 (see Data). There are no data on the effects of atogepant on the breastfed infant or the effects on milk production. The developmental and health benefits of breastfeeding should be considered along with the mother’s clinical need for QULIPTA and any potential adverse effects on the breastfed infant from QULIPTA or from the underlying maternal condition.

Data

A study was conducted in twelve healthy adult lactating females who were between 23 and 34 years of age and between 1 month and 6 months postpartum. Each subject was administered a single oral dose of atogepant 60 mg. Maternal plasma and breast milk were collected for 24 hours after dosing. Using a 150 mL/kg/day estimated infant milk intake, the mean estimated relative infant dose was approximately 0.19% of the maternal weight-adjusted dose. The mean milk-to-plasma ratio was 0.08. All subjects had detectable levels of atogepant in breast milk during the study; by 16 to 24 hours after dosing, 25% of females in the study had detectable levels of atogepant in breast milk. The mean cumulative amount of atogepant excreted in breast milk over 24 hours was less than 0.01 mg of a 60 mg dose.

8.4 Pediatric Use

Safety and effectiveness in pediatric patients have not been established.

8.5 Geriatric Use

Population pharmacokinetic modeling suggests no clinically significant pharmacokinetic differences between elderly and younger subjects. Clinical studies of QULIPTA did not include sufficient numbers of patients aged 65 years and over to determine whether they respond differently from younger patients. In general, dose selection for an elderly patient should be cautious, usually starting at the low end of the dosing range reflecting the greater frequency of decreased hepatic, renal, or cardiac function, and of concomitant disease or other drug therapy.

8.6 Renal Impairment

The renal route of elimination plays a minor role in the clearance of atogepant [see Clinical Pharmacology (12.3)]. For episodic migraine, in patients with severe renal impairment (CLcr 15-29 mL/min) and in patients with end-stage renal disease (ESRD) (CLcr <15 mL/min), the recommended dosage of QULIPTA is 10 mg once daily; in patients with ESRD undergoing intermittent dialysis, QULIPTA should preferably be taken after dialysis [see Dosage and Administration (2.2)]. For chronic migraine, use of QULIPTA in patients with severe renal impairment and in patients with ESRD is not recommended. No dose adjustment is recommended for patients with mild or moderate renal impairment.

8.7 Hepatic Impairment

No dose adjustment of QULIPTA is recommended for patients with mild or moderate hepatic impairment. Avoid use of QULIPTA in patients with severe hepatic impairment [see Adverse Reactions (6.1) and Clinical Pharmacology (12.3)].

11 DESCRIPTION

The active ingredient of QULIPTA is atogepant, a calcitonin gene-related peptide (CGRP) receptor antagonist. The chemical name of atogepant is (3’S)-N-[(3S,5S,6R)-6-methyl-2-oxo-1-(2,2,2-trifluoroethyl)-5-(2,3,6-trifluorophenyl)piperidin-3-yl]-2’-oxo-1’,2’,5,7-tetrahydrospiro[cyclopenta[b]pyridine-6,3’-pyrrolo[2,3-b]pyridine]-3-carboxamide, and it has the following structural formula:

The molecular formula is C29H23F6N5O3 and molecular weight is 603.5. Atogepant is a white to off-white powder. It is freely soluble in ethanol, soluble in methanol, sparingly soluble in acetone, slightly soluble in acetonitrile, and practically insoluble in water.

QULIPTA is available as tablets for oral administration containing 10 mg, 30 mg, or 60 mg atogepant. The inactive ingredients include colloidal silicon dioxide, croscarmellose sodium, mannitol, microcrystalline cellulose, polyvinylpyrrolidone vinyl acetate copolymer, sodium chloride, sodium stearyl fumarate, and vitamin E polyethylene glycol succinate.

12 CLINICAL PHARMACOLOGY

12.1 Mechanism of Action

Atogepant is a calcitonin gene-related peptide (CGRP) receptor antagonist.

12.2 Pharmacodynamics

Cardiac Electrophysiology

At a dose 5 times the maximum recommended daily dose, QULIPTA does not prolong the QT interval to any clinically relevant extent.

12.3 Pharmacokinetics

Absorption

Following oral administration of QULIPTA, atogepant is absorbed with peak plasma concentrations at approximately 1 to 2 hours. Atogepant displays dose-proportional pharmacokinetics up to 170 mg per day (approximately 3 times the highest recommended dosage), with no accumulation.

Effect of Food

When QULIPTA was administered with a high-fat meal, the food effect was not significant (AUC and Cmax were reduced by approximately 18% and 22%, respectively, with no effect on median time to maximum atogepant plasma concentration). QULIPTA was administered without regard to food in clinical efficacy studies.

Distribution

Plasma protein binding of atogepant was not concentration-dependent in the range of 0.1 to 10 µM; the unbound fraction of atogepant was approximately 4.7% in human plasma. The mean apparent volume of distribution of atogepant (Vz/F) after oral administration is approximately 292 L.

Elimination

Metabolism

Atogepant is eliminated mainly through metabolism, primarily by CYP3A4. The parent compound (atogepant), and a glucuronide conjugate metabolite (M23) were the most prevalent circulating components in human plasma.

Excretion

The elimination half-life of atogepant is approximately 11 hours. The mean apparent oral clearance (CL/F) of atogepant is approximately 19 L/hr. Following single oral dose of 50 mg ^14C-atogepant to healthy male subjects, 42% and 5% of the dose was recovered as unchanged atogepant in feces and urine, respectively.

Specific Populations

Patients with Renal Impairment

The renal route of elimination plays a minor role in the clearance of atogepant. Based on a population pharmacokinetic analysis, there is no significant difference in the pharmacokinetics of atogepant in patients with mild or moderate renal impairment (CLcr 30-89 mL/min) relative to those with normal renal function (CLcr >90 mL/min). Patients with severe renal impairment or end-stage renal disease (ESRD; CLcr <30 mL/min) have not been studied [see Dosage and Administration (2.2) and Use in Specific Populations (8.6)].

Patients with Hepatic Impairment

In patients with pre-existing mild (Child-Pugh Class A), moderate (Child-Pugh Class B), or severe (Child-Pugh Class C) hepatic impairment, the total atogepant exposure was increased by 24%, 15%, and 38%, respectively. Due to a potential for liver injury in patients with severe hepatic impairment, avoid use of QULIPTA in patients with severe hepatic impairment [see Use in Specific Populations (8.7)].

Other Specific Populations

Based on a population pharmacokinetic analysis, age, sex, race, and body weight did not have a significant effect on the pharmacokinetics (Cmax and AUC) of atogepant. Therefore, no dose adjustments are warranted based on these factors.

Drug Interactions

In Vitro Studies

Enzymes

In vitro, atogepant is not an inhibitor for CYPs 3A4, 1A2, 2B6, 2C8, 2C9, 2C19, or 2D6 at clinically relevant concentrations. Atogepant does not inhibit MAO-A or UGT1A1 at clinically relevant concentrations. Atogepant is not anticipated to be a clinically significant perpetrator of drug-drug interactions through CYP450s, MAO-A, or UGT1A1 inhibition.

Atogepant is not an inducer of CYP1A2, CYP2B6, or CYP3A4 at clinically relevant concentrations.

Transporters

Atogepant is a substrate of P-gp, BCRP, OATP1B1, OATP1B3, and OAT1. Dose adjustment for concomitant use of QULIPTA with inhibitors of OATP is recommended based on a clinical interaction study with a OATP inhibitor [see Dosage and Administration (2.2)].

Coadministration of atogepant with BCRP and/or P-gp inhibitors is not expected to increase the exposure of atogepant. Atogepant is not a substrate of OAT3, OCT2, or MATE1.

Atogepant is not an inhibitor of P-gp, BCRP, OAT1, OAT3, NTCP, BSEP, MRP3, or MRP4 at clinically relevant concentrations. Atogepant is a weak inhibitor of OATP1B1, OATP1B3, OCT1, and MATE1. No clinical drug interactions are expected for atogepant as a perpetrator with these transporters.

In Vivo Studies

CYP3A4 Inhibitors

Co-administration of QULIPTA with itraconazole, a strong CYP3A4 inhibitor, resulted in a clinically significant increase (Cmax by 2.15-fold and AUC by 5.5-fold) in the exposure of atogepant in healthy subjects [see Drug Interactions (7.1)].

Physiologically based pharmacokinetic (PBPK) modeling suggested co-administration of QULIPTA with moderate or weak CYP3A4 inhibitors increase atogepant AUC by 1.7- and 1.1-fold, respectively. The changes in atogepant exposure when coadministered with weak or moderate CYP3A4 inhibitors are not expected to be clinically significant.

CYP3A4 Inducers

Co-administration of QULIPTA with rifampin, a strong CYP3A4 inducer, decreased atogepant AUC by 60% and Cmax by 30% in healthy subjects [see Drug Interactions (7.2)]. The observed change in atogepant exposures is a composite effect of inhibition of OATP1B1 and OATP1B3 transporters as well as induction of CYP3A4 and P-gp. No dedicated drug interaction studies were conducted to assess concomitant use with moderate CYP3A4 inducers. Moderate inducers of CYP3A4 can decrease atogepant exposure [see Drug Interactions (7.2)]. Co-administration of QULIPTA with topiramate, a weak inducer of CYP3A4, decreased atogepant mean steady-state AUC 0-τ by 25% and mean steady-state Cmax by 24% in healthy subjects [see Drug Interactions (7.2)].

BCRP/OATP/P-gp Inhibitors

Co-administration of QULIPTA with single dose rifampin, an OATP inhibitor, increased atogepant AUC by 2.85-fold and Cmax by 2.23-fold in healthy subjects [see Drug Interactions (7.3)].

Co-administration of QULIPTA with quinidine, a P-gp inhibitor, increased atogepant AUC by 26% and Cmax by 4% in healthy subjects. The changes in atogepant exposure when co-administered with P-gp inhibitors are not expected to be clinically significant.

PBPK modeling suggests that co-administration of QULIPTA with BCRP inhibitors increases atogepant exposure by 1.2-fold. This increase is not expected to be clinically significant.

Other Drug Interaction Evaluations

Co-administration of QULIPTA with oral contraceptive components ethinyl estradiol and levonorgestrel, famotidine, esomeprazole, acetaminophen, naproxen, sumatriptan, or ubrogepant did not result in significant pharmacokinetic interactions for either atogepant or co-administered drugs. Co-administration of QULIPTA with topiramate did not result in clinically significant changes in the pharmacokinetics of topiramate.

13 NONCLINICAL TOXICOLOGY

13.1 Carcinogenesis, Mutagenesis, Impairment of Fertility

Carcinogenicity

Atogepant was administered orally to mice (0, 5, 20, or 75 mg/kg/day in males; 0, 5, 30, 160 mg/kg/day in females) and rats (0, 10, 20, or 100 mg/kg in males; 0, 25, 65, or 200 mg/kg in females) for up to 2 years. There was no evidence of drug-related tumors in either species. Plasma exposures at the highest doses tested in mice and rats were approximately 8 and 20-35 times, respectively, that in humans at the maximum recommended human dose (MRHD) of 60 mg/day.

Mutagenicity

Atogepant was negative in in vitro (Ames, chromosomal aberration test in Chinese Hamster Ovary cells) and in vivo (rat bone marrow micronucleus) assays.

Impairment of Fertility

Oral administration of atogepant (0, 5, 20, or 125 mg/kg/day) to male and female rats prior to and during mating and continuing in females to Gestation Day 7 resulted in no adverse effects on fertility or reproductive performance. Plasma exposures (AUC) at the highest dose tested are approximately 15 times that in humans at the MRHD.

14 CLINICAL STUDIES

14.1 Episodic Migraine

The efficacy of QULIPTA for the preventive treatment of episodic migraine in adults was demonstrated in two randomized, multicenter, double-blind, placebo-controlled studies (Study 1 and Study 2). The studies enrolled patients with at least a 1-year history of migraine with or without aura, according to the International Classification of Headache Disorders (ICHD-3) diagnostic criteria.

In Study 1 (NCT03777059), 910 patients were randomized 1:1:1:1 to receive QULIPTA 10 mg (N = 222), QULIPTA 30 mg (N = 230), QULIPTA 60 mg (N = 235), or placebo (N = 223), once daily for 12 weeks. In Study 2 (NCT02848326), 652 patients were randomized 1:2:2:2 to receive QULIPTA 10 mg (N = 94), QULIPTA 30 mg (N = 185), QULIPTA 60 mg (N = 187), or placebo (N = 186), once daily for 12 weeks. In both studies, patients were allowed to use acute headache treatments (i.e., triptans, ergotamine derivatives, NSAIDs, acetaminophen, and opioids) as needed. The use of a concomitant medication that acts on the CGRP pathway was not permitted for either acute or preventive treatment of migraine. The studies excluded patients with myocardial infarction, stroke, or transient ischemic attacks within six months prior to screening.

Study 1

The primary efficacy endpoint was the change from baseline in mean monthly migraine days (MMD) across the 12-week treatment period. Secondary endpoints included the change from baseline in mean monthly headache days, the change from baseline in mean monthly acute medication use days, the proportion of patients achieving at least a 50% reduction from baseline in mean MMD (3-month average), the change from baseline in mean monthly Activity Impairment in Migraine-Diary (AIM-D) Performance of Daily Activities (PDA) domain scores, the change from baseline in mean monthly AIM-D Physical Impairment (PI) domain scores, across the 12-week treatment period, and the change from baseline at Week 12 for Migraine Specific Quality of Life Questionnaire version 2.1 (MSQ v2.1) Role Function-Restrictive (RFR) domain scores.

The AIM-D evaluates difficulty with performance of daily activities (PDA domain) and physical impairment (PI domain) due to migraine, with scores ranging from 0 to 100. Higher scores indicate greater impact of migraine, and reductions from baseline indicate improvement. The MSQ v2.1 Role Function-Restrictive (RFR) domain score assesses how often migraine impacts function related to daily social and work-related activities over the past 4 weeks, with scores ranging from 0 to 100. Higher scores indicate lesser impact of migraine on daily activities, and increases from baseline indicate improvement.

Patients had a mean age of 42 years (range 18 to 73 years), 89% were female, 83% were White, 14% were Black, and 9% were of Hispanic or Latino ethnicity. The mean migraine frequency at baseline was approximately 8 migraine days per month and was similar across treatment groups. A total of 805 (88%) patients completed the 12-week double-blind study period. Key efficacy results of Study 1 are summarized in Table 3.

Table 3: Efficacy Endpoints in Study 1
 | QULIPTA 10 mg N=214 | QULIPTA 30 mg N=223 | QULIPTA 60 mg N=222 | Placebo N=214
Monthly Migraine Days (MMD) across 12 weeks
Baseline | 7.5 | 7.9 | 7.8 | 7.5
Mean change from baseline | -3.7 | -3.9 | -4.2 | -2.5
Difference from placebo | -1.2 | -1.4 | -1.7
p-value | <0.001 | <0.001 | <0.001
Monthly Headache Days across 12 weeks
Baseline | 8.4 | 8.8 | 9.0 | 8.4
Mean change from baseline | -3.9 | -4.0 | -4.2 | -2.5
Difference from placebo | -1.4 | -1.5 | -1.7
p-value | <0.001 | <0.001 | <0.001
Monthly Acute Medication Use Days across 12 weeks
Baseline | 6.6 | 6.7 | 6.9 | 6.5
Mean change from baseline | -3.7 | -3.7 | -3.9 | -2.4
Difference from placebo | -1.3 | -1.3 | -1.5
p-value | <0.001 | <0.001 | <0.001
≥ 50% MMD Responders across 12 weeks
% Responders | 56 | 59 | 61 | 29
Difference from placebo (%) | 27 | 30 | 32
p-value | <0.001 | <0.001 | <0.001
MSQ v2.1 RFR Domain* at week 12
Baseline | 44.9 | 44.0 | 46.8 | 46.8
Mean change from baseline | 30.4 | 30.5 | 31.3 | 20.5
Difference from placebo | 9.9 | 10.1 | 10.8
p-value | <0.001 | <0.001 | <0.001
AIM-D PDA Domain** across 12 weeks
Baseline | 15.5 | 16.9 | 15.9 | 15.2
Mean change from baseline | -7.3 | -8.6 | -9.4 | -6.1
Difference from placebo | -1.2 | -2.5 | -3.3
p-value | NS† | <0.001 | <0.001
AIM-D PI Domain*** across 12 weeks
Baseline | 11.7 | 13.0 | 11.6 | 11.2
Mean change from baseline | -5.1 | -6.0 | -6.5 | -4.0
Difference from placebo | -1.1 | -2.0 | -2.5
p-value | NS† | 0.002 | <0.001
* Migraine Specific Quality of Life Questionnaire version 2.1 Role Function-Restrictive domain score
** Activity Impairment in Migraine-Diary Performance of Daily Activities domain score
*** Activity Impairment in Migraine-Diary Physical Impairment domain score
†Not statistically significant (NS)

Figure 1 shows the mean change from baseline in MMD in Study 1. Patients treated with QULIPTA had greater mean decreases from baseline in MMD across the 12-week treatment period compared to patients who received placebo.

Figure 1: Change from Baseline in Monthly Migraine Days in Study 1

Figure 2 shows the distribution of change from baseline in mean MMD across the 12-week treatment period, in 2-day increments, by treatment group. A treatment benefit over placebo for all doses of QULIPTA is seen across a range of mean changes from baseline in MMD.

Figure 2: Distribution of Change from Baseline in Mean Monthly Migraine Days by Treatment Group in Study 1

Study 2

The primary efficacy endpoint was the change from baseline in mean monthly migraine days across the 12-week treatment period.

Patients had a mean age of 40 years (range: 18 to 74 years), 87% were female, 76% were White, 20% were Black, and 15% were of Hispanic or Latino ethnicity. The mean migraine frequency at baseline was approximately 8 migraine days per month. A total of 541 (83%) patients completed the 12-week double-blind study period.

In Study 2, there was a significantly greater reduction in mean monthly migraine days across the 12-week treatment period in all three QULIPTA treatment groups, compared with placebo, as summarized in Table 4.

Table 4: Efficacy Endpoints in Study 2
 | QULIPTA 10 mg N=92 | QULIPTA 30 mg N=182 | QULIPTA 60 mg N=177 | Placebo N=178
Monthly Migraine Days (MMD) across 12 weeks
Baseline | 7.6 | 7.6 | 7.7 | 7.8
Mean change from baseline | -4.0 | -3.8 | -3.6 | -2.8
Difference from placebo | -1.1 | -0.9 | -0.7
p-value | 0.024 | 0.039 | 0.039
Monthly Headache Days across 12 weeks
Baseline | 8.9 | 8.7 | 8.9 | 9.1
Mean change from baseline | -4.3 | -4.2 | -3.9 | -2.9
Difference from placebo | -1.4 | -1.2 | -0.9
p-value | 0.024 | 0.039 | 0.039

Figure 3 shows the mean change from baseline in MMD in Study 2. Patients treated with QULIPTA had greater mean decreases from baseline in MMD across the 12-week treatment period compared to patients who received placebo.

Figure 3: Change from Baseline in Monthly Migraine Days in Study 2

Figure 4 shows the distribution of change from baseline in mean MMD across the 12-week treatment period, in 2-day increments, by treatment group. A treatment benefit over placebo for all doses of QULIPTA is seen across a range of mean changes from baseline in MMD.

Figure 4: Distribution of Change from Baseline in Mean Monthly Migraine Days by Treatment Group in Study 2

14.2 Chronic Migraine

Study 3

The efficacy of QULIPTA for the preventive treatment of chronic migraine in adults was demonstrated in a randomized, multicenter, double-blind, placebo-controlled study (Study 3). The study enrolled patients with at least a 1-year history of chronic migraine, according to the ICHD-3 diagnostic criteria.

Study 3 (NCT03855137) included randomization of patients to QULIPTA 60 mg once daily (N = 262) or placebo (N = 259) for 12 weeks. A subset of patients (11%) was allowed to use one concomitant migraine preventive medication. Patients were allowed to use acute headache treatments (i.e., triptans, ergotamine derivatives, NSAIDs, acetaminophen, and opioids) as needed. Patients with medication overuse headache also were enrolled. The use of a concomitant medication that acts on the CGRP pathway was not permitted for either acute or preventive treatment of migraine. The study excluded patients with myocardial infarction, stroke, or transient ischemic attacks within six months prior to screening.

The primary efficacy endpoint was the change from baseline in mean MMD across the 12-week treatment period. Secondary endpoints included the change from baseline in mean monthly headache days, the change from baseline in mean monthly acute medication use days, the proportion of patients achieving at least a 50% reduction from baseline in mean MMD (3-month average), the change from baseline in mean monthly AIM-D PDA domain scores, the change from baseline in mean monthly AIM-D PI domain scores, across the 12-week treatment period, and the change from baseline at Week 12 for MSQ v2.1 RFR domain scores.

Patients had a mean age of 42 years (range 18 to 74 years), 87% were female, 60% were White, 3% were Black, 36% were Asian, and 4% were of Hispanic or Latino ethnicity. The mean migraine frequency at baseline was approximately 19 migraine days per month and was similar across treatment groups. A total of 463 (89%) of these patients completed the 12-week double-blind study period.
Key efficacy results of Study 3 are summarized in Table 5.

Table 5: Efficacy Endpoints in Study 3
 | QULIPTA 60 mg QD N=256 | Placebo N=246
Monthly Migraine Days (MMD) across 12 weeks
Baseline | 19.2 | 18.9
Mean change from baseline | -6.9 | -5.1
Difference from placebo | -1.8
p-value | <0.001
Monthly Headache Days across 12 weeks
Baseline | 21.5 | 21.4
Mean change from baseline | -7.0 | -5.1
Difference from placebo | -1.9
p-value | <0.001
Monthly Acute Medication Use Days across 12 weeks
Baseline | 15.5 | 15.4
Mean change from baseline | -6.2 | -4.1
Difference from placebo | -2.1
p-value | <0.001
≥ 50% MMD Responders across 12 weeks
% Responders | 41 | 26
Difference from placebo (%) | 15
p-value | <0.001
MSQ v2.1 RFR Domain* at week 12
Baseline | 43.4 | 43.9
Mean change from baseline | 23.3 | 17.2
Difference from placebo | 6.2
p-value | <0.001
AIM-D PDA Domain** across 12 weeks
Baseline | 31.2 | 29.5
Mean change from baseline | -12.8 | -9.4
Difference from placebo | -3.4
p-value | <0.001
AIM-D PI Domain*** across 12 weeks
Baseline | 27.1 | 25.2
Mean change from baseline | -10.6 | -7.9
Difference from placebo | -2.7
p-value | 0.003

* Migraine Specific Quality of Life Questionnaire version 2.1 Role Function-Restrictive domain score

** Activity Impairment in Migraine-Diary Performance of Daily Activities domain score

*** Activity Impairment in Migraine-Diary Physical Impairment domain score

Figure 5 shows the mean change from baseline in MMD in Study 3. Patients treated with QULIPTA had greater mean decreases from baseline in MMD across the 12-week treatment period compared to patients who received placebo.

Figure 5: Change from Baseline in Monthly Migraine Days in Study 3

Figure 6 shows the distribution of change from baseline in mean MMD across the 12-week treatment period, in 2-day increments, by treatment group. A treatment benefit of QULIPTA over placebo is seen across a range of mean changes from baseline in MMD.

Figure 6: Distribution of Change from Baseline in Mean Monthly Migraine Days by Treatment Group in Study 3

16 HOW SUPPLIED/STORAGE AND HANDLING

16.1 How Supplied

QULIPTA 10 mg is supplied as white to off-white, round biconvex tablets debossed with “A” and “10” on one side in the following packaging presentations:

- Bottle of 30, NDC: 0074-7095-30

QULIPTA 30 mg is supplied as white to off-white, oval biconvex tablets debossed with “A30” on one side in the following packaging presentations:

- Bottle of 30, NDC: 0074-7096-30

QULIPTA 60 mg is supplied as white to off-white, oval biconvex tablets debossed with “A60” on one side in the following packaging presentations:

- Bottle of 30, NDC: 0074-7094-30

16.2 Storage and Handling

Store between 20°C and 25°C (68°F and 77°F): excursions permitted between 15°C and 30°C (59°F and 86°F) [see USP Controlled Room Temperature].

17 PATIENT COUNSELING INFORMATION

Advise the patient to read the FDA-approved patient labeling (Patient Information).

Hypersensitivity Reactions

Inform patients about the signs and symptoms of hypersensitivity reactions and that these reactions can occur with QULIPTA. Advise patients to discontinue QULIPTA and seek immediate medical attention if they experience any symptoms of a hypersensitivity reaction [see Warnings and Precautions (5.1)].

Hypertension

Inform patients that hypertension can develop or pre-existing hypertension can worsen with QULIPTA, and that they should contact their healthcare providers if they experience elevation in their blood pressure [see Warnings and Precautions (5.2)].

Raynaud’s Phenomenon

Inform patients that Raynaud’s phenomenon can develop or worsen with QULIPTA. Advise patients to discontinue QULIPTA and contact their healthcare provider if they experience signs or symptoms of Raynaud’s phenomenon [see Warnings and Precautions (5.3)].

Drug Interactions

Inform patients that QULIPTA may interact with certain other drugs, and that dosage modifications of QULIPTA may be recommended when used with some other drugs. Advise patients to report to their healthcare provider the use of any other prescription medications, over-the-counter medications, herbal products, or grapefruit juice [see Dosage and Administration (2.2) and Drug Interactions (7.1, 7.2, 7.3)].

Pregnancy

Advise patients to notify their healthcare provider if they become pregnant during treatment or plan to become pregnant. Encourage pregnant patients to enroll in the registry that monitors pregnancy outcomes in women exposed to QULIPTA during pregnancy [see Use in Specific Populations (8.1)].

Lactation

Inform patients to notify their healthcare provider if they are breastfeeding or plan to breastfeed [see Use in Specific Populations (8.2)].

Manufactured for:
AbbVie Inc.
North Chicago, IL 60064

© 2025 AbbVie. All rights reserved.

QULIPTA and its design are trademarks of Allergan Pharmaceuticals International Limited, an AbbVie company.
20096809 September 2025

PATIENT INFORMATION
QULIPTA® (kew-LIP-tah)
(atogepant)
tablets, for oral use

What is QULIPTA?

- QULIPTA is a prescription medicine used for the preventive treatment of migraine in adults.

It is not known if QULIPTA is safe and effective in children.

Do not take QULIPTA if you:

- have had an allergic reaction to atogepant or any ingredients in QULIPTA. See the end of this Patient Information leaflet for a complete list of ingredients in QULIPTA.

Before you take QULIPTA tell your healthcare provider about all of your medical conditions, including if you:

- have high blood pressure.
- have circulation problems in your fingers and toes.
- have kidney problems or are on dialysis.
- have liver problems.
- are pregnant or plan to become pregnant. It is not known if QULIPTA will harm your unborn baby.
  - Pregnancy Registry: There is a pregnancy registry for women who take QULIPTA. The purpose of this registry is to collect information about the health of you and your baby. Talk to your healthcare provider or call 1-833-277-0206 to enroll in this registry. You can also visit http://empresspregnancyregistry.com.
- are breastfeeding or plan to breastfeed. Very small amounts of QULIPTA pass into breast milk. Talk to your healthcare provider if you plan to breastfeed.

Tell your healthcare provider about all the medicines you take, including prescription and over-the-counter medicines, vitamins, and herbal supplements. QULIPTA may affect the way other medicines work, and other medicines may affect how QULIPTA works. Your healthcare provider may need to change the dose of QULIPTA when taken with certain other medicines.

Keep a list of medicines you take to show to your healthcare provider or pharmacist when you get a new medicine.

How should I take QULIPTA?

- Take QULIPTA by mouth with or without food.
- Take QULIPTA exactly as your healthcare provider tells you to take it.

What are the possible side effects of QULIPTA?
QULIPTA can cause serious side effects, including:

- Allergic (hypersensitivity) reactions, including anaphylaxis: Serious allergic reactions can happen when you take QULIPTA or days after. Stop taking QULIPTA and get emergency medical help right away if you get any of the following symptoms, which may be part of a serious allergic reaction:

• swelling of the face, lips, or tongue
• trouble breathing
• rash

- itching
- hives

- High blood pressure: High blood pressure or worsening of high blood pressure can happen when you take QULIPTA. Contact your healthcare provider if you have an increase in blood pressure.
- Raynaud’s phenomenon: A type of circulation problem can worsen or happen when you take QULIPTA. Raynaud’s phenomenon can lead to your fingers or toes feeling numb, cool, or painful, or changing color from pale, to blue, to red. Contact your healthcare provider if these symptoms occur.

The most common side effects of QULIPTA include: nausea, constipation, and fatigue/sleepiness.
These are not all of the possible side effects of QULIPTA. Call your doctor for medical advice about side effects. You may report side effects to FDA at 1-800-FDA-1088.

How should I store QULIPTA?

- Store QULIPTA at room temperature between 68ºF to 77ºF (20ºC to 25ºC).

Keep QULIPTA and all medicines out of the reach of children.

General information about the safe and effective use of QULIPTA.
Medicines are sometimes prescribed for purposes other than those listed in a Patient Information leaflet. Do not use QULIPTA for a condition for which it was not prescribed. Do not give QULIPTA to other people, even if they have the same symptoms you have. It may harm them. You can ask your pharmacist or healthcare provider for information about QULIPTA that is written for health professionals.

What are the ingredients in QULIPTA?
Active ingredient: atogepant
Inactive ingredients: colloidal silicon dioxide, croscarmellose sodium, mannitol, microcrystalline cellulose, polyvinylpyrrolidone vinyl acetate copolymer, sodium chloride, sodium stearyl fumarate, and vitamin E polyethylene glycol succinate.
Manufactured for:
AbbVie Inc.
North Chicago, IL 60064
© 2025 AbbVie. All rights reserved.
QULIPTA and its design are trademarks of Allergan Pharmaceuticals International Limited, an AbbVie company.

This Patient Information has been approved by the U.S. Food and Drug Administration Revised: 6/2025

20096809

PRINCIPAL DISPLAY PANEL

NDC 0074-7095-30
Rx Only
QULIPTA®
(atogepant) tablets
10 mg
Contains 30 Tablets

PRINCIPAL DISPLAY PANEL

NDC 0074-7096-30
Rx Only
QULIPTA®
(atogepant) tablets
30 mg
Contains 30 Tablets

PRINCIPAL DISPLAY PANEL

NDC 0074-7094-30
Rx Only
QULIPTA®
(atogepant) tablets
60 mg
Contains 30 Tablets